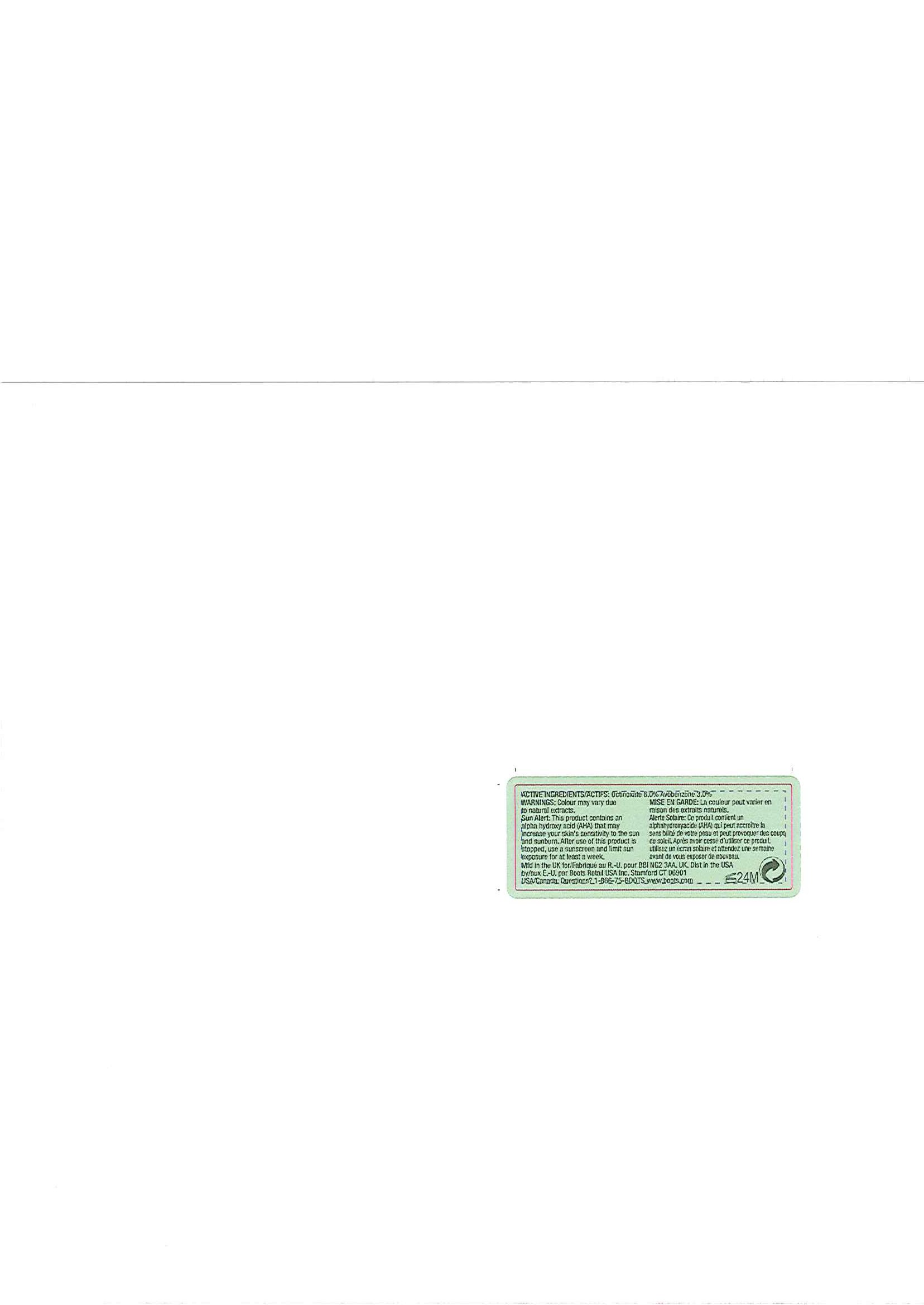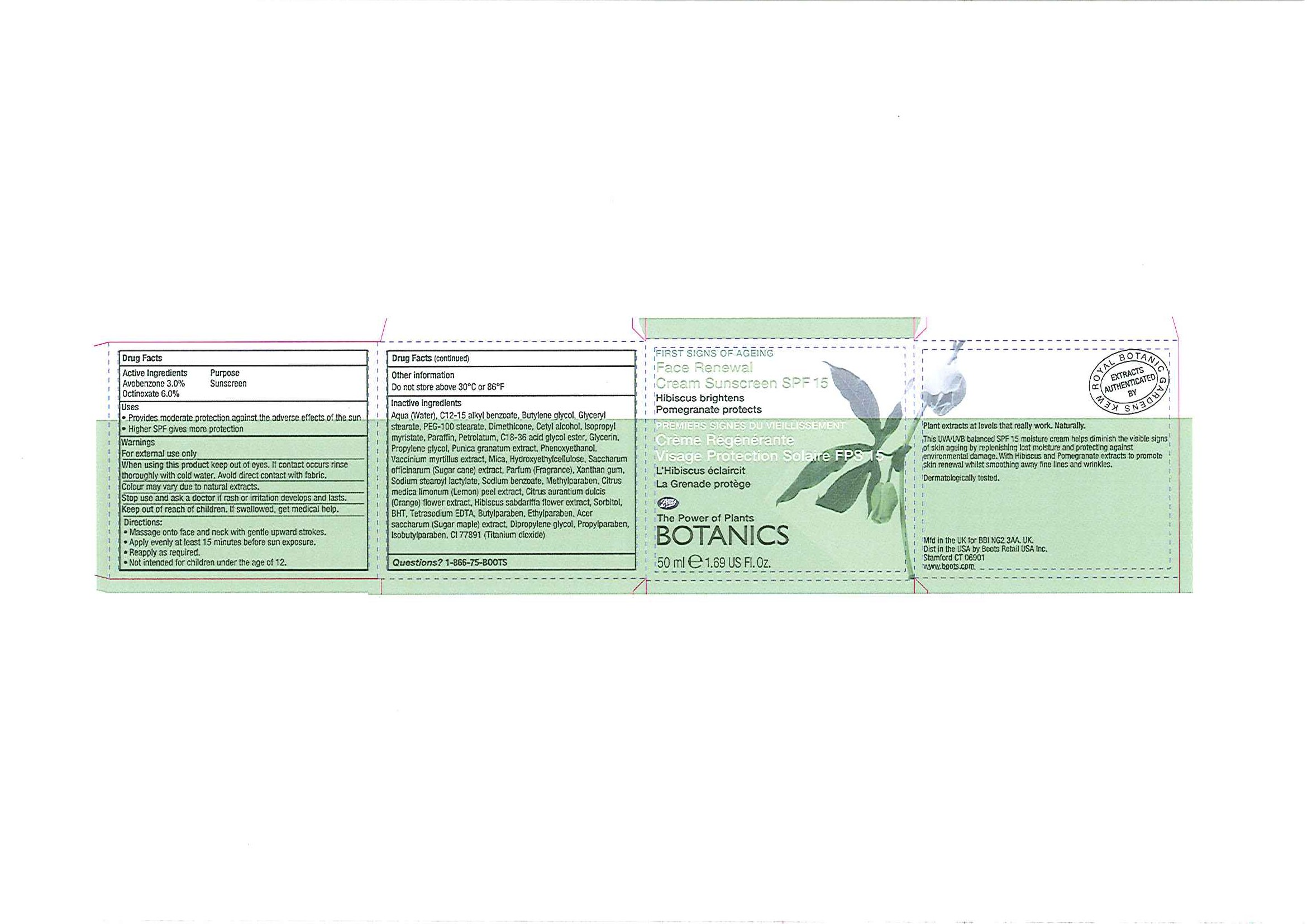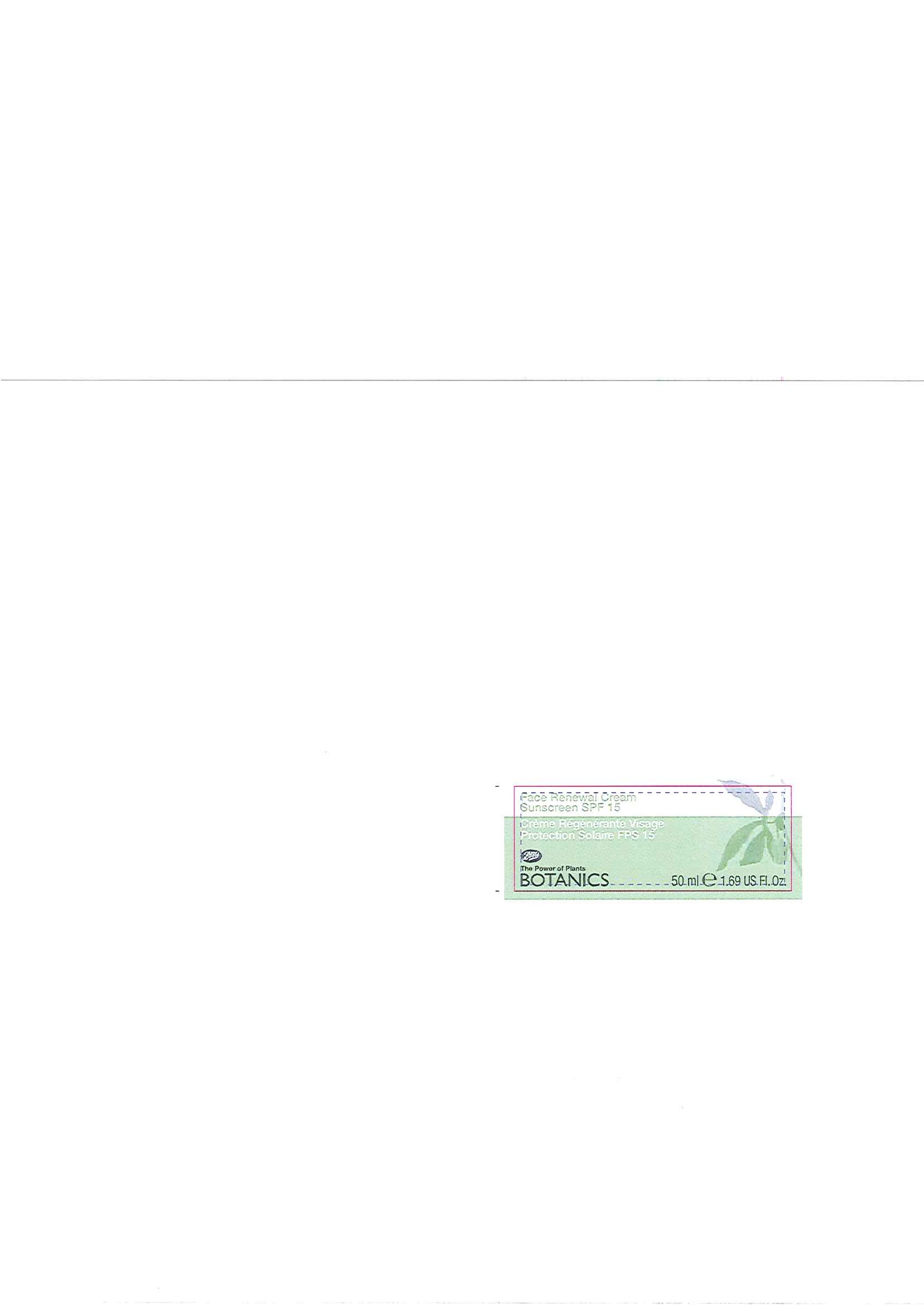 DRUG LABEL: BOTANICS FACE RENEWAL SUNSCREEN SPF 15
NDC: 11489-057 | Form: CREAM
Manufacturer: BCM Ltd
Category: otc | Type: HUMAN OTC DRUG LABEL
Date: 20101207

ACTIVE INGREDIENTS: OCTINOXATE 3.0 mL/50 mL; AVOBENZONE 1.5 mL/50 mL
INACTIVE INGREDIENTS: WATER; BUTYLENE GLYCOL; GLYCERYL MONOSTEARATE; POLYOXYL 100 STEARATE; DIMETHICONE; CETYL ALCOHOL; ISOPROPYL MYRISTATE; PARAFFIN; PETROLATUM; GLYCERIN; PROPYLENE GLYCOL; POMEGRANATE; PHENOXYETHANOL; BILBERRY; SUGARCANE; XANTHAN GUM; SODIUM BENZOATE; METHYLPARABEN; LEMON JUICE; ORANGE; SORBITOL; BUTYLATED HYDROXYANISOLE; BUTYLPARABEN; ETHYLPARABEN; MAPLE SYRUP; PROPYLPARABEN; ISOBUTYLPARABEN

Carton and jar labelling

ACTIVE INGREDIENT

BOTANICS FACE RENEWAL CREAM SUNSCREEN SPF 15

Active Ingredients Purpose

Avobenzone 3.0% Sunscreens

Octinoxate 6.0%

Uses

- Provides moderate protection against the adverse effects of the sun
- Higher SPF gives more protection

Warnings

For external use only

When using this product keep out of eyes. If contact occurs rinse thoroughly with cold water. Avoid direct contact with fabric.

HOW SUPPLIED

Colour may vary due to natural extracts

Stop use and ask a doctor if rash or irritation develops and lasts.

Keep out of reach of children. If swallowed, get medical help.

DIRECTIONS

- Massage onto face and neck with gentle upward strokes.
- Apply evenly at least 15 minutes before sun exposure.
- Reapply as required.
- Not intended for children under the age of 12.

Other Information

Do not store above 30^0C or 86^0F

Inactive Ingredients

Aqua (Water), C12-15 alkyl benzoate, Butylene glycol, Glyceryl stearate, PEG-100 stearate, Dimethicone, Cetyl alcohol, Isopropyl myristate, Paraffin, Petrolatum, C18-36 acid glycol ester, Glycerin, Propylene glycol, Punica granatum extract, Phenoxyethanol, Vaccinium myrtillus extract, Mica, Hydroxyethylcellulose, Saccharum officinarum (Sugar cane) extract, Parfum (Fragrance), Xanthan gum, Sodium stearoyl lactylate, Sodium benzoate, Methylparaben, Citrus medica limonum (Lemon) peel extract, Citrus aurantium dulcis (Orange) flower extract, Hibiscus sabdariffa flower extract, Sorbitol, BHT, Tetrasodium EDTA, Butylparaben, Ethylparaben, Acer saccharum (Sugar maple) extract, Dipropylene glycol, Propylparaben, Isobutylparaben, CI 77891 (Titanium dixoide)

Questions? 1-866-75-BOOTS

DESCRIPTION

Plant extracts at levels that really work. Naturally.

This UVA/UVB balanced SPF 15 moisture cream helps diminish the visible signs of skin ageing by replenishing lost moisture and protecting against environmental damage. With Hibiscus and Pomegranate extracts to promote skin renewal whilst smoothing away fine lines and wrinkles.

Dermatologically tested.

PATIENT COUNSELING INFORMATION

Mfd in the U.K. for BBI NG2 3AA. UK.

Dist in the USA by Boots Retail USA Inc.

Stamford CT 06901

www.boots.com

Carton label

FIRST SIGNS OF AGEING

Face Renewal Cream Sunscreen SPF 15

Hibiscus brightens

Pomegranate protects

PREMIERS SIGNES DU VIEILLISSEMENT

Crème Régénérante Visage Protection Solaire FPS 15

L'Hibiscus éclaircit

La Grenade protège

Boots

The Power of Plants

BOTANICS

50ml e 1.69 US Fl. Oz

Face Renewal Cream carton.jpg

Jar front label

Face Renewal Cream Sunscreen SPF 15

Crème Régénérante Visage Protection Solaire FPS 15

Boots

The Power of Plants

BOTANICS

50ml e 1.69 US Fl. Oz

Face Renewal Cream front label.jpg

Jar back label

ACTIVE INGREDIENTS/ACTIFS: Octinoxate 6.0% Avobenzone 3.0%

WARNINGS: Colour may vary due to natural extracts.

Sun Alert: This product contains an alpha hydroxy acid (AHA) that may increase your skin's sensitivity to the sun and sunburn. After use of this product is stopped, use a sunscreen and limit sun exposure for at least a week.

MISE EN GARDE: La couleur peut varier en raison des extraits naturels.

Alert Solaire: Ce produit contient un alphahydroxyacide (AHA) qui peut accroître la sensibilité de votre peau et peut provoquer des coupe de soleil. Après avoir cessé d'utiliser ce produit, utilisez un écran solaire et attendez une semaine avant de vous exposure de nouveau.

Mdf in the U.K. for/Fabriqué au R.-U. pour BBI NG2 3AA. UK.

Dist in the USA by/aux É.-U. par Boots Retail USA Inc. Stamford CT 06901

USA/Canada: Questions? 1-866-75-BOOTS

www.boots.com

Face Renewal Cream back label.jpg